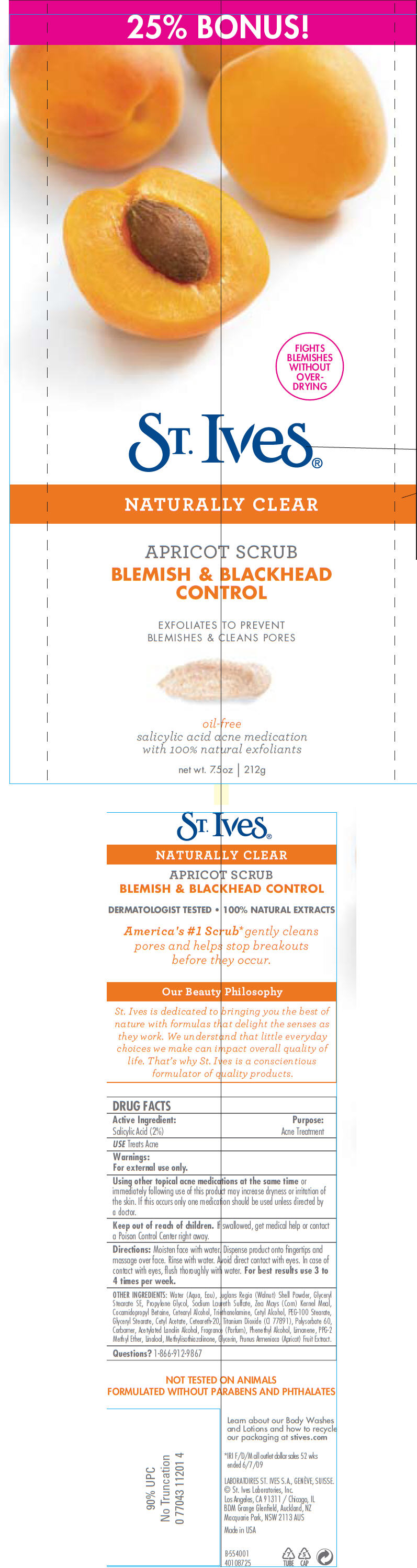 DRUG LABEL: St. Ives Blemish and Blackhead control
NDC: 54726-0100 | Form: EMULSION
Manufacturer: Cosmetic Laboratories of America 
Category: otc | Type: HUMAN OTC DRUG LABEL
Date: 20110302

ACTIVE INGREDIENTS: Salicylic Acid 0.02 g/1 g
INACTIVE INGREDIENTS: Water; juglans regia shell; Glyceryl Monostearate; Propylene Glycol; Corn Meal; Cetostearyl Alcohol; Sodium Laureth Sulfate; Glycerin; Cocamidopropyl Betaine; Cetyl Alcohol; Trolamine; PEG-100 Stearate; Titanium Dioxide; Apricot Seed Oil; Polysorbate 60; Polyoxyl 20 Cetostearyl Ether; Phenylethyl Alcohol; Methylisothiazolinone

ST. Ives®
NATURALLY CLEAR
APRICOT SCRUB
BLEMISH & BLACKHEAD
CONTROL

DRUG FACTS

Active Ingredient

Salicylic Acid (2%)

Purpose

Acne Treatment

USE

Treats Acne

Warnings

For external use only.

WHEN USING

Using other topical acne medications at the same time or immediately following use of this product may increase dryness or irritation of the skin. If this occurs only one medication should be used unless directed by a doctor.

Keep out of reach of children. If swallowed, get medical help or contact a Poison Control Center right away.

Directions

Moisten face with water. Dispense product onto fingertips and massage over face. Rinse with water. Avoid direct contact with eyes. In case of contact with eyes, flush thoroughly with water. For best results use 3 to 4 times per week.

OTHER INGREDIENTS

Water (Aqua, Eau), Juglans Regia (Walnut) Shell Powder, Glyceryl Stearate SE, Propylene Glycol, Sodium Laureth Sulfate, Zea Mays (Corn) Kernel Meal, Cocamidopropyl Betaine, Cetearyl Alcohol, Triethanolamine, Cetyl Alcohol, PEG-100 Stearate, Glyceryl Stearate, Cetyl Acetate, Ceteareth-20, Titanium Dioxide (CI 77891), Polysorbate 60, Carbomer, Acetylated Lanolin Alcohol, Fragrance (Parfum), Phenethyl Alcohol, Limonene, PPG-2 Methyl Ether, Linalool, Methylisothiazolinone, Glycerin, Prunus Armeniaca (Apricot) Fruit Extract.

Questions?

1-866-912-9867

PRINCIPAL DISPLAY PANEL - 212 g Tube Label

25% BONUS!

FIGHTS
BLEMISHES
WITHOUT
OVER-
DRYING

ST. Ives®

NATURALLY CLEAR

APRICOT SCRUB
BLEMISH & BLACKHEAD
CONTROL

EXFOLIATES TO PREVENT
BLEMISHES & CLEANS PORES

oil-free
salicylic acid acne medication
with 100% natural exfoliants

net wt. 7.5oz | 212g